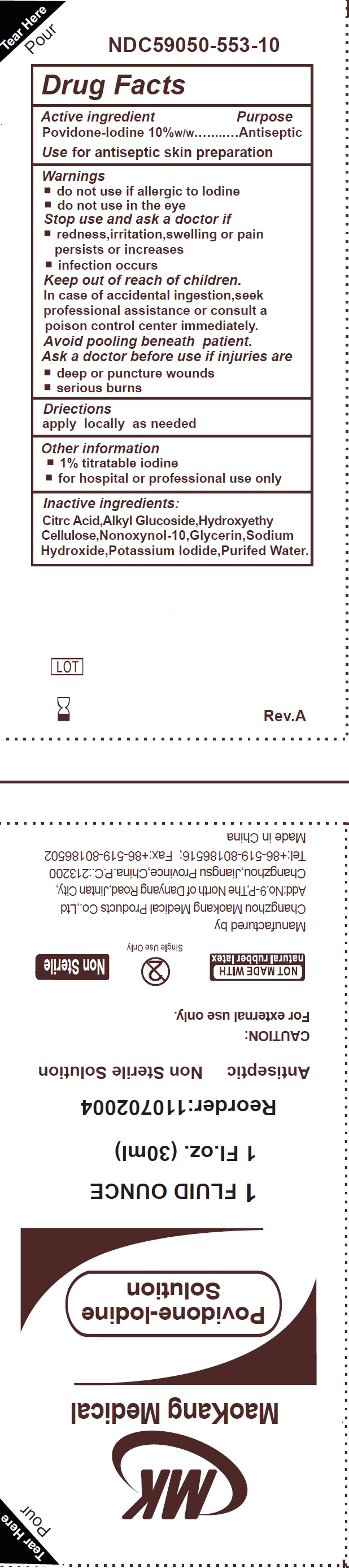 DRUG LABEL: Non-sterile
NDC: 59050-553 | Form: PATCH
Manufacturer: Changzhou Maokang Medical Products Co., Ltd
Category: otc | Type: HUMAN OTC DRUG LABEL
Date: 20250828

ACTIVE INGREDIENTS: POVIDONE-IODINE 10 g/100 g
INACTIVE INGREDIENTS: CITRIC ACID MONOHYDRATE; NONOXYNOL-10; GLYCERIN; SODIUM HYDROXIDE; POTASSIUM IODIDE; WATER

Povidone-Iodine Solution, Non-sterile

Active ingredient

Povidone-lodine 10%w/w

Purpose

Antiseptic

Use

for antiseptic skin preparation

Warnings

do not use

- if allergic to lodine
- do not use in the eye

Stop use and ask a doctor if

- redness, irritation, swelling or pain persists or increases
- infection occurs

Keep out of reach of children.

In case of accidental ingestion, seek professional assistance or consult a poison control center immediately.

Avoid pooling beneath patient.

Ask a doctor before use if injuries are

- deep or puncture wounds
- serious burns

Driections

apply locally as needed

Other information

- 1% titratable iodine
- for hospital or professional use only

Inactive ingredients:

Citrc Acid, Alkyl Glucoside, Hydroxyethy, Cellulose, Nonoxynol-10, Glycerin, Sodium Hydroxide, Potassium lodide, Purifed Water.